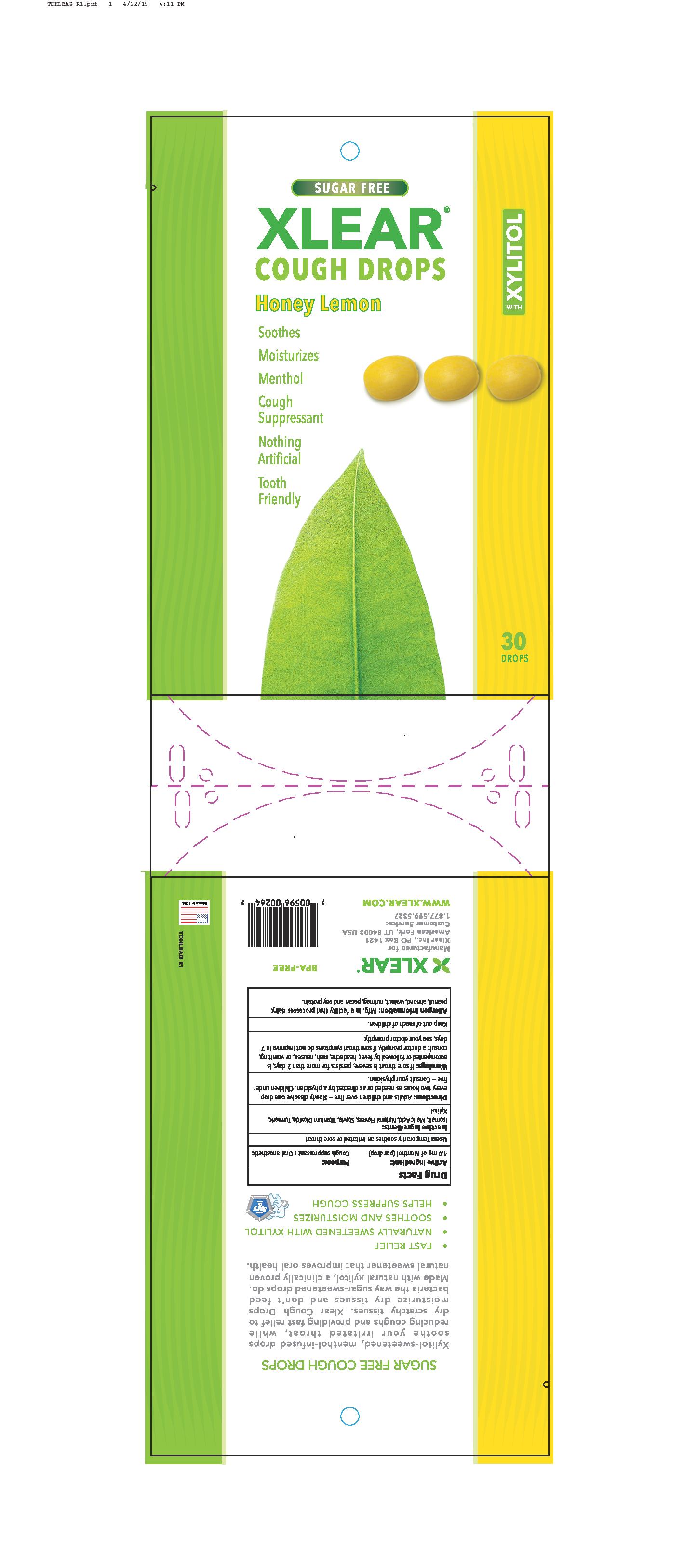 DRUG LABEL: Xlear Cough Drops (Honey Lemon)
NDC: 27017-022 | Form: LOZENGE
Manufacturer: Xlear Inc.
Category: otc | Type: HUMAN OTC DRUG LABEL
Date: 20230110

ACTIVE INGREDIENTS: MENTHOL 4 mg/1 1
INACTIVE INGREDIENTS: XYLITOL; ISOMALT; HONEY; CURCUMA LONGA LEAF; TITANIUM DIOXIDE; MALIC ACID; STEVIA LEAF

Xlear Cough Drops (Honey Lemon)

ACTIVE INGREDIENT

4.0 mg of Menthol (per drop)

PURPOSE

Cough Suppressant / Oral Anesthetic

INDICATIONS AND USAGE

Temporarily soothes an irritated or sore throat

DOSAGE AND ADMINISTRATION

Adults and children over five - Slowly dissolve one drop every two hours as needed or as directed by a physician. Children under five - Consult your physician.

WARNINGS

If sore throat is severe, persists for more than 2 days, is accompanied or followed by fever, headache, rash, nausea, or vomiting, consult a doctor promptly. If sore throat symptoms do not improve in 7 days, see your doctor promptly

Keep out of reach of children.

OTHER SAFETY INFORMATION

Allergen Information: Mfg. in a facility that processes dairy, peanut, almond, walnut, nutmeg, pecan, and soy protein.

INACTIVE INGREDIENT

cinnamon bark oil, clove bud oil, eucalyptus radiata leaf oil, isomalt, lemon peel oil, pectin, peppermint aerial parts oil, rosemary leaf oil, stevia leaf extract, water